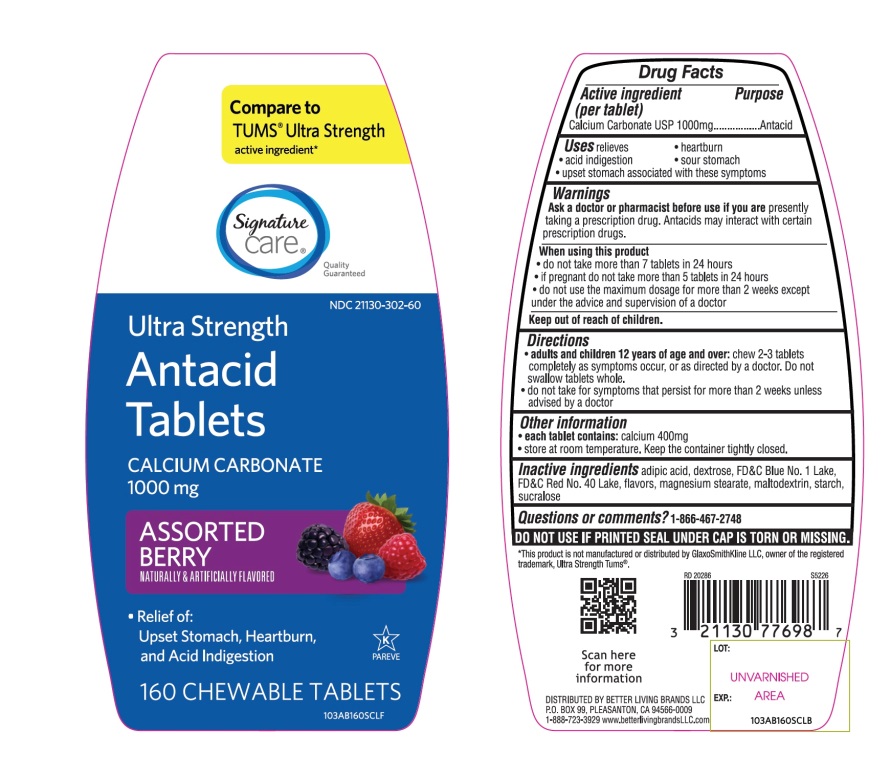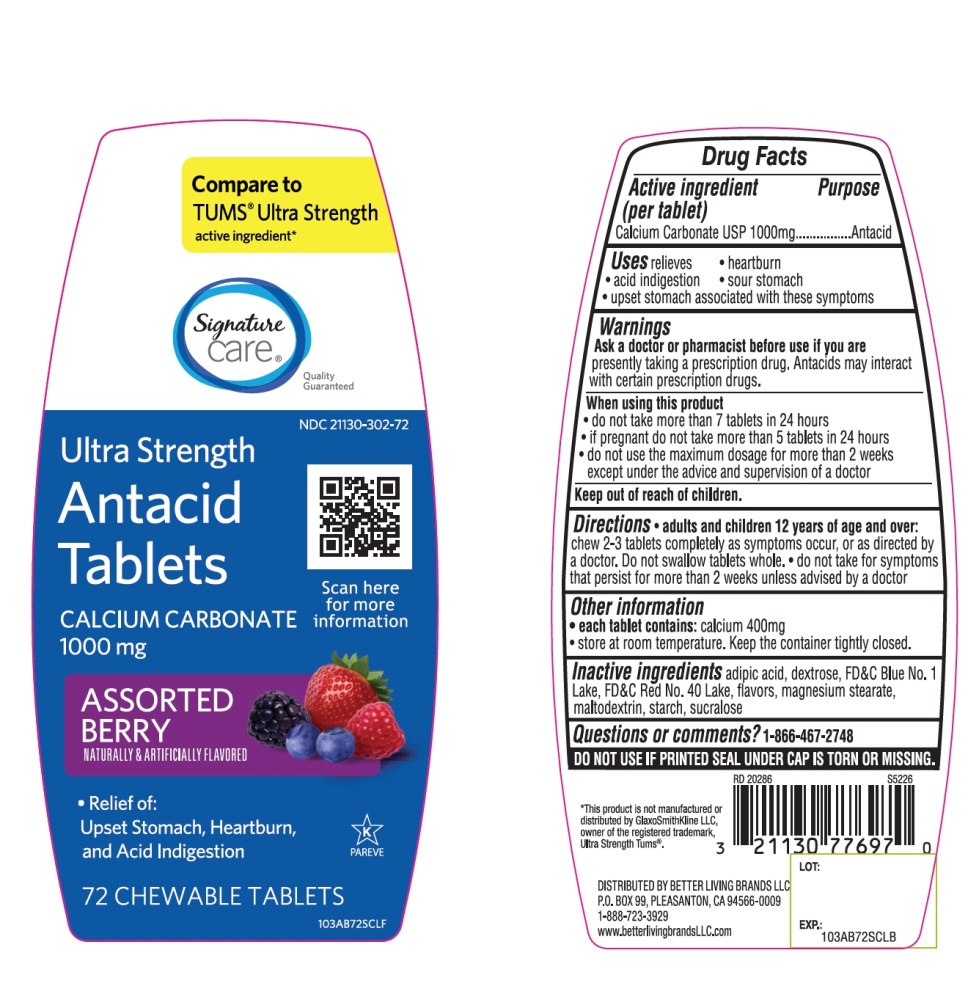 DRUG LABEL: Ultra Strength
NDC: 21130-302 | Form: TABLET, CHEWABLE
Manufacturer: BETTER LIVING BRANDS LLC
Category: otc | Type: HUMAN OTC DRUG LABEL
Date: 20251029

ACTIVE INGREDIENTS: CALCIUM CARBONATE 1000 mg/1 1
INACTIVE INGREDIENTS: ADIPIC ACID; DEXTROSE, UNSPECIFIED FORM; FD&C BLUE NO. 1; FD&C RED NO. 40; MAGNESIUM STEARATE; MALTODEXTRIN; STARCH, CORN; SUCRALOSE

Ultra Strength Antacid Calcium Carbonate Drug Facts

Active ingredient (per tablet)

Calcium Carbonate USP 1000mg

Purpose

Antacid

Uses

relieves

- heartburn
- acid indigestion
- sour stomach
- upset stomach associated with these symptoms

Ask a doctor or pharmacist before use if you are

presently taking a prescription drug. Antacids may interact with certain prescription drugs.

When using this product

- do not take more than 7 tablets in 24 hours
- if pregnant do not take more than 5 tablets in 24 hours
- do not use the maximum dosage for more than 2 weeks except under the advice and supervision of a doctor

Directions

- adults and children 12 years of age and over:chew 2-3 tablets as symptoms occur, or as directed by a doctor. Do not swallow tablets whole.
- do not take for symptoms that persist for more than 2 weeks unless advised by a doctor

Other information

- each tablet contains:elemental calcium 400mg
- store at room temperature. Keep the container tightly closed.

Inactive ingredients

adipic acid, dextrose, FD&C Blue No. 1, FD&C Red No. 40, flavors, magnesium stearate, maltodextrin, starch, sucralose.

Questions or comments?

1-866-467-2748

DO NOT USE IF PRINTED SEAL UNDER CAP IS TORN OR MISSING

Package/Label Principal Display Panel

*Compare to the active ingredient Ultra Strength Tums®

ULTRA STRENGTH

Antacid Tablets

CALCIUM CARBONATE 1000 mg

Fast Relief of Upset Stomach, Heartburn, Acid Indigestion

Assorted Berry Flavors

Naturally and Artificially Flavored

GLUTEN FREE

K PAREVE

Distributed by:

*This product is not manufactured or distributed by GlaxoSmithKline LLC, owner of the registered trademark, Ultra Strength Tums®.